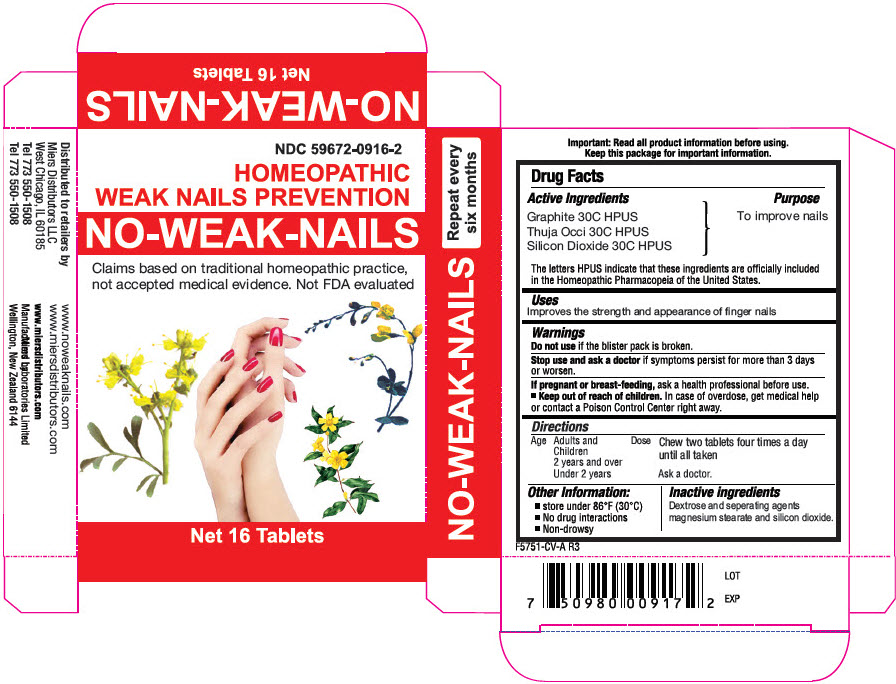 DRUG LABEL: NO-WEAK-NAILS
NDC: 59672-0916 | Form: TABLET
Manufacturer: Miers Laboratories
Category: homeopathic | Type: HUMAN OTC DRUG LABEL
Date: 20250109

ACTIVE INGREDIENTS: GRAPHITE 30 [hp_C]/1 1; THUJA OCCIDENTALIS LEAFY TWIG 30 [hp_C]/1 1; SILICON DIOXIDE 30 [hp_C]/1 1
INACTIVE INGREDIENTS: DEXTROSE, UNSPECIFIED FORM 242 mg/1 1; Magnesium stearate

NO-WEAK-NAILS

Drug Facts

Active Ingredients

Graphite 30C HPUS
Thuja Occi 30C HPUS
Silicon Dioxide 30C HPUS

The letters HPUS indicate that these ingredients are officially included in the Homeopathic Pharmacopeia of the United States.

Purpose

To improve nails

Uses

Improves the strength and appearance of finger nails

Warnings

Do not use if the blister pack is broken.

Ask a doctor before use in children under 2 years of age.

Stop use and ask a doctor if symptoms persist for more than 3 days or worsen.

PREGNANCY OR BREAST FEEDING

If pregnant or breast-feeding, ask a health professional before use.

Keep out of reach of children. In case of overdose, get medical help or contact a Poison Control Center right away.

Directions

Age | Dose
Adults and Children 2 years and over | Chew two tablets four times a day for two days until all taken.
Under 2 years | Ask a doctor.

Other Information

- Store under 86°F (30°C)
- No drug interactions
- Non-drowsy

Inactive ingredients

Dextrose and separating agents magnesium stearate and silicon dioxide

PRINCIPAL DISPLAY PANEL - 16 Tablet Blister Pack Carton

NDC 59672-0916-2

HOMEOPATHIC
WEAK NAILS PREVENTION

NO-WEAK-NAILS

Claims based on traditional homeopathic practice,
not accepted medical evidence. Not FDA evaluated

Net 16 Tablets